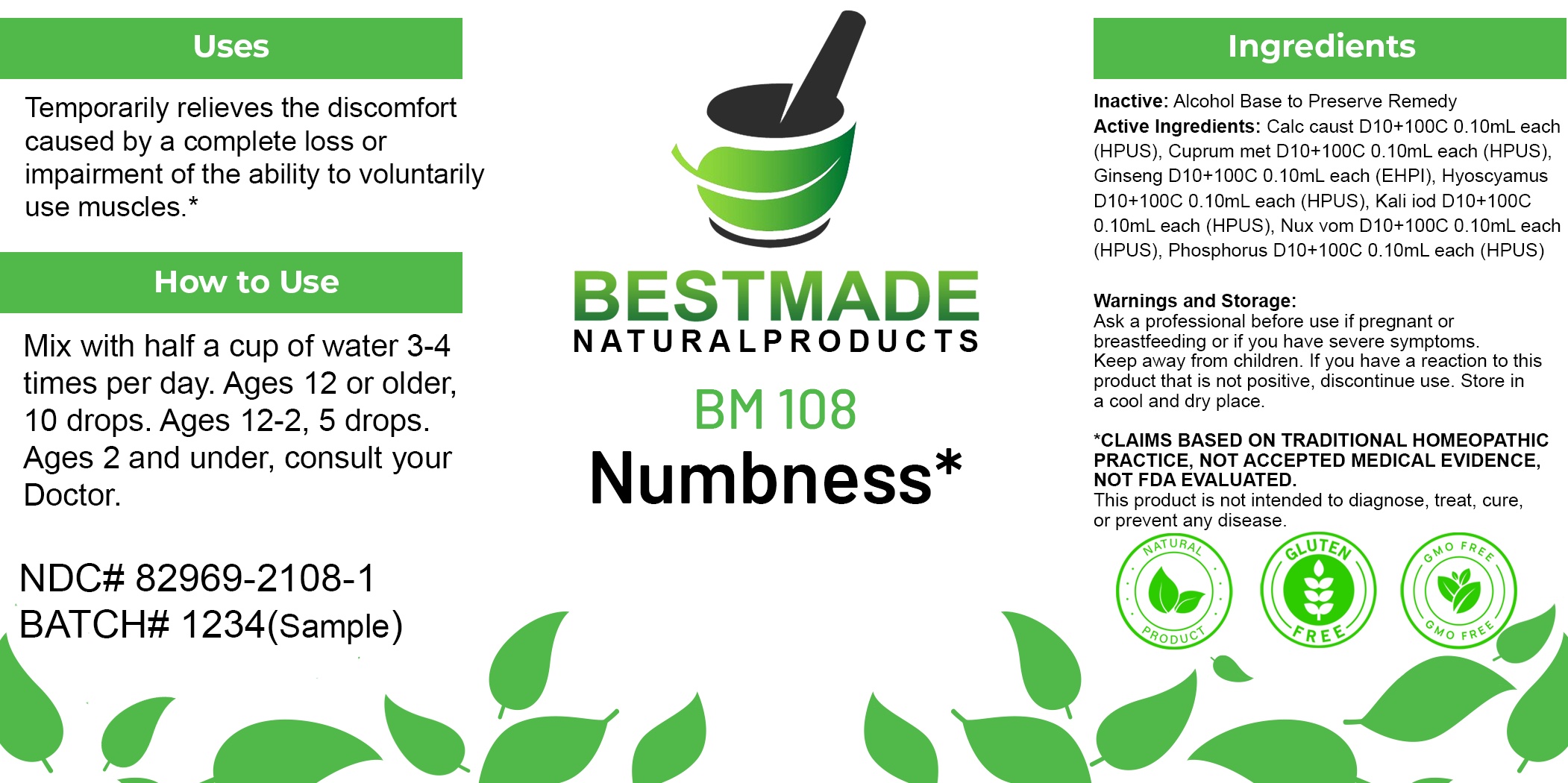 DRUG LABEL: Bestmade Natural Products BM108
NDC: 82969-2108 | Form: LIQUID
Manufacturer: Bestmade Natural Products
Category: homeopathic | Type: HUMAN OTC DRUG LABEL
Date: 20250207

ACTIVE INGREDIENTS: STRYCHNOS NUX-VOMICA SEED 30 [hp_C]/30 [hp_C]; COPPER 30 [hp_C]/30 [hp_C]; AMERICAN GINSENG 30 [hp_C]/30 [hp_C]; CALCIUM HYDROXIDE 30 [hp_C]/30 [hp_C]; POTASSIUM IODIDE 30 [hp_C]/30 [hp_C]; PHOSPHORUS 30 [hp_C]/30 [hp_C]; HYOSCYAMUS NIGER 30 [hp_C]/30 [hp_C]
INACTIVE INGREDIENTS: ALCOHOL 30 [hp_C]/30 [hp_C]

BM108

DOSAGE AND ADMINISTRATION

How to Use

Mix with half a cup of water 3-4 times per day. Ages 12 or older, 10 drops. Ages 12-2, 5 drops. Ages 2 and under, consult your Doctor.

Inactive:

Alcohol Base to Preserve Product

Active Ingredients:

Calc caust D10+100C 0.10mL each (HPUS), Cuprum met D10+100C 0.10mL each (HPUS), Ginseng D10+100C 0.10mL each (EHPI), Hyoscyamus D10+100C 0.10mL each (HPUS), Kali iod D10+100C 0.10mL each (HPUS), Nux vom D10+100C 0.10mL each (HPUS), Phosphorus D10+100C 0.10mL each (HPUS)

Uses
Temporarily relieves the discomfort caused by a complete loss or impairment of the ability to voluntarily use muscles.*

Uses
Temporarily relieves the discomfort caused by a complete loss or impairment of the ability to voluntarily use muscles.*

KEEP OUT OF REACH OF CHILDREN

Warnings and Storage:

Ask a professional before use if pregnant or breastfeeding or if you have severe symptoms.

Keep away from children. If you have a reaction to this product that is not positive, discontinue use. Store in a cool and dry place

*CLAIMS BASED ON TRADITIONAL HOMEOPATHIC PRACTICE, NOT ACCEPTED MEDICAL EVIDENCE NOT FDA EVALUATED.
This product is not intended to diagnose, treat, cure, or prevent any disease.

Warnings and Storage:

Ask a professional before use if pregnant or breastfeeding or if you have severe symptoms.

Keep away from children. If you have a reaction to this product that is not positive, discontinue use. Store in a cool and dry place

*CLAIMS BASED ON TRADITIONAL HOMEOPATHIC PRACTICE, NOT ACCEPTED MEDICAL EVIDENCE NOT FDA EVALUATED.
This product is not intended to diagnose, treat, cure, or prevent any disease.

Entire package label